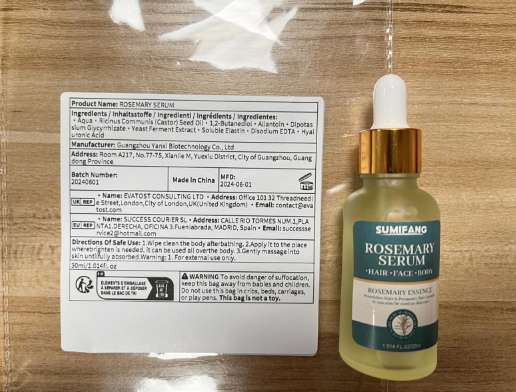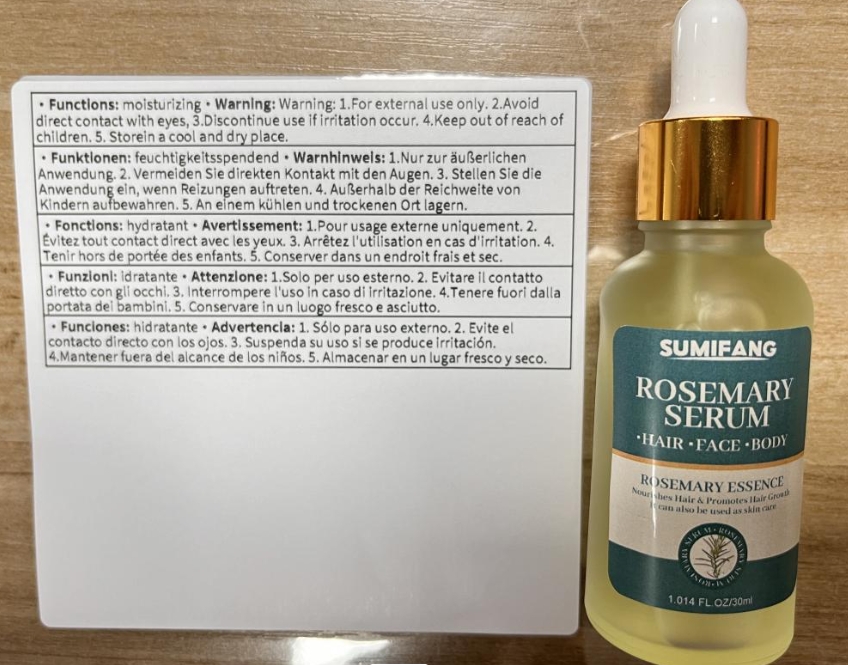 DRUG LABEL: ROSEMARY SERUM
NDC: 84025-082 | Form: CREAM
Manufacturer: Guangzhou Yanxi Biotechnology Co., Ltd
Category: otc | Type: HUMAN OTC DRUG LABEL
Date: 20240723

ACTIVE INGREDIENTS: ALLANTOIN 3 mg/100 mL; 1,2-BUTANEDIOL 5 mg/100 mL
INACTIVE INGREDIENTS: WATER

DOSAGE AND ADMINISTRATION

1.Wipe clean the body afterbathing. 2.Apply it to the placewherebrighten is needed, it can be used all overthe body

WARNINGS

keep put of children

INACTIVE INGREDIENT

Aqua

INDICATIONS AND USAGE

The skin is dark and dehydrated

keep out of children

PURPOSE

Brightens and moisturizes skin